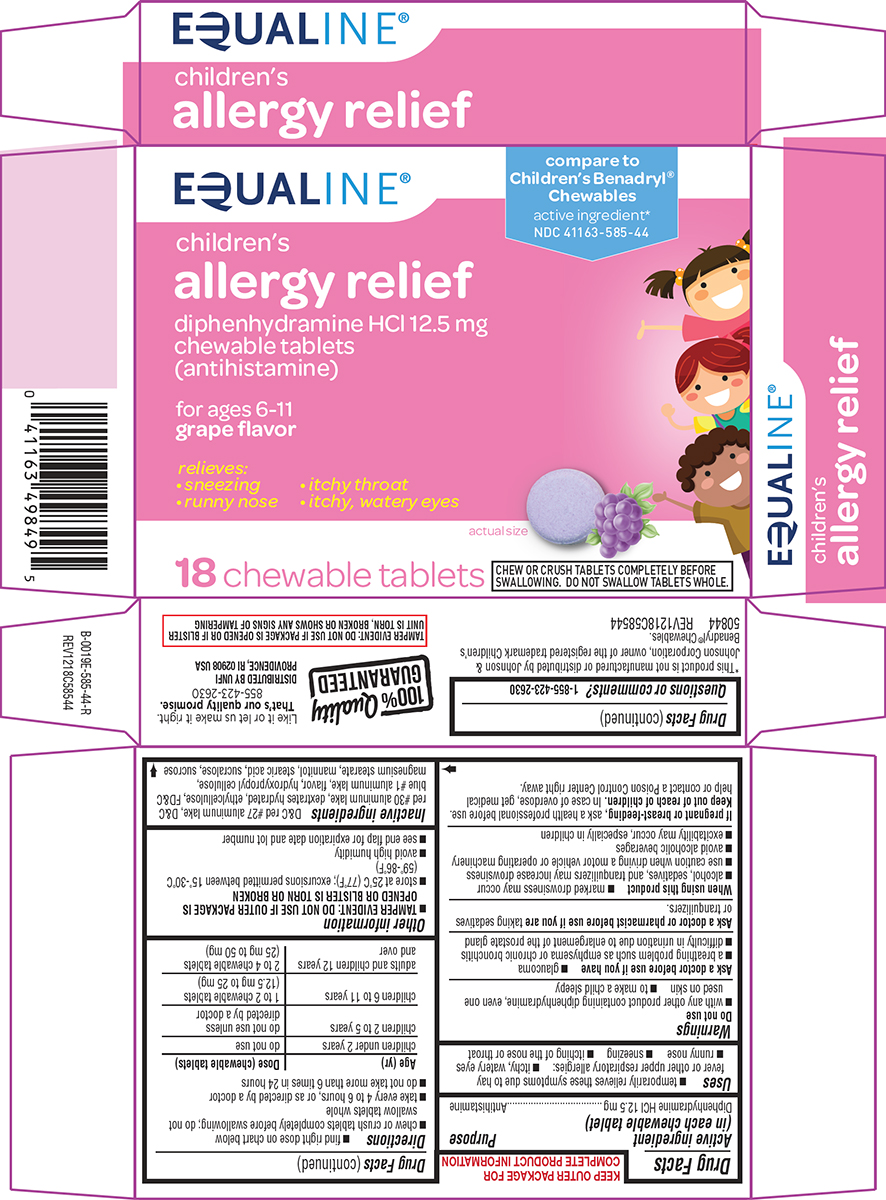 DRUG LABEL: allergy relief
NDC: 41163-585 | Form: TABLET, CHEWABLE
Manufacturer: United Natural Foods, Inc. dba UNFI
Category: otc | Type: HUMAN OTC DRUG LABEL
Date: 20250916

ACTIVE INGREDIENTS: DIPHENHYDRAMINE HYDROCHLORIDE 12.5 mg/1 1
INACTIVE INGREDIENTS: D&C RED NO. 27 ALUMINUM LAKE; D&C RED NO. 30 ALUMINUM LAKE; DEXTROSE MONOHYDRATE; ETHYLCELLULOSE, UNSPECIFIED; FD&C BLUE NO. 1 ALUMINUM LAKE; HYDROXYPROPYL CELLULOSE, UNSPECIFIED; MAGNESIUM STEARATE; MANNITOL; STEARIC ACID; SUCRALOSE; SUCROSE

Equaline 44-585 Delisted

Active ingredient (in each chewable tablet)

Diphenhydramine HCl 12.5 mg

Purpose

Antihistamine

Uses

- temporarily relieves these symptoms due to hay fever or other upper respiratory allergies:
  - itchy, watery eyes
  - runny nose
  - sneezing
  - itching of the nose or throat

Warnings

Do not use

- with any other product containing diphenhydramine, even one used on skin
- to make a child sleepy

Ask a doctor before use if you have

- glaucoma
- a breathing problem such as emphysema or chronic bronchitis
- difficulty in urination due to enlargement of the prostate gland

Ask a doctor or pharmacist before use if you are

taking sedatives or tranquilizers.

When using this product

- marked drowsiness may occur
- alcohol, sedatives, and tranquilizers may increase drowsiness
- use caution when driving a motor vehicle or operating machinery
- avoid alcoholic beverages
- excitability may occur, especially in children

If pregnant or breast-feeding,

ask a health professional before use.

Keep out of reach of children.

In case of overdose, get medical help or contact a Poison Control Center right away.

Directions

- find right dose on chart below
- chew or crush tablets completely before swallowing; do not swallow tablets whole
- take every 4 to 6 hours, or as directed by a doctor
- do not take more than 6 times in 24 hours

Age (yr) | Dose (chewable tablets)
children under 2 years | do not use
children 2 to 5 years | do not use unless directed by a doctor
children 6 to 11 years | 1 to 2 chewable tablets (12.5 mg to 25 mg)
adults and children 12 years and over | 2 to 4 chewable tablets (25 mg to 50 mg)

Other information

- TAMPER EVIDENT: DO NOT USE IF OUTER PACKAGE IS OPENED OR BLISTER IS TORN OR BROKEN
- store at 25°C (77°F); excursions permitted between 15°-30°C (59°-86°F)
- avoid high humidity
- see end flap for expiration date and lot number

Inactive ingredients

D&C red #27 aluminum lake, D&C red #30 aluminum lake, dextrates hydrated, ethylcellulose, FD&C blue #1 aluminum lake, flavor, hydroxypropyl cellulose, magnesium stearate, mannitol, stearic acid, sucralose, sucrose

Questions or comments?

1-855-423-2630

Principal Display Panel

EQUALINE®

compare to
Children’s Benadryl®
Chewables
active ingredient*

NDC 41163-585-44

children's
allergy relief
diphenhydramine HCl 12.5 mg
chewable tablets
(antihistamine)

for ages 6-11
grape flavor

relieves:
• sneezing • itchy throat
• runny nose • itchy, watery eyes

18 chewable tablets

actual size

CHEW OR CRUSH TABLETS COMPLETELY BEFORE SWALLOWING.
DO NOT SWALLOW TABLETS WHOLE.

TAMPER EVIDENT: DO NOT USE IF PACKAGE IS OPENED OR IF BLISTER
UNIT IS TORN, BROKEN OR SHOWS ANY SIGNS OF TAMPERING

*This product is not manufactured or distributed by Johnson &
Johnson Corporation, owner of the registered trademark Children’s
Benadryl® Chewables.
50844 REV1218C58544

100% Quality
GUARANTEED

Like it or let us make it right.
That’s our quality promise.
855-423-2630

DISTRIBUTED BY UNFI
PROVIDENCE, RI 02908 USA

Equaline 44-585